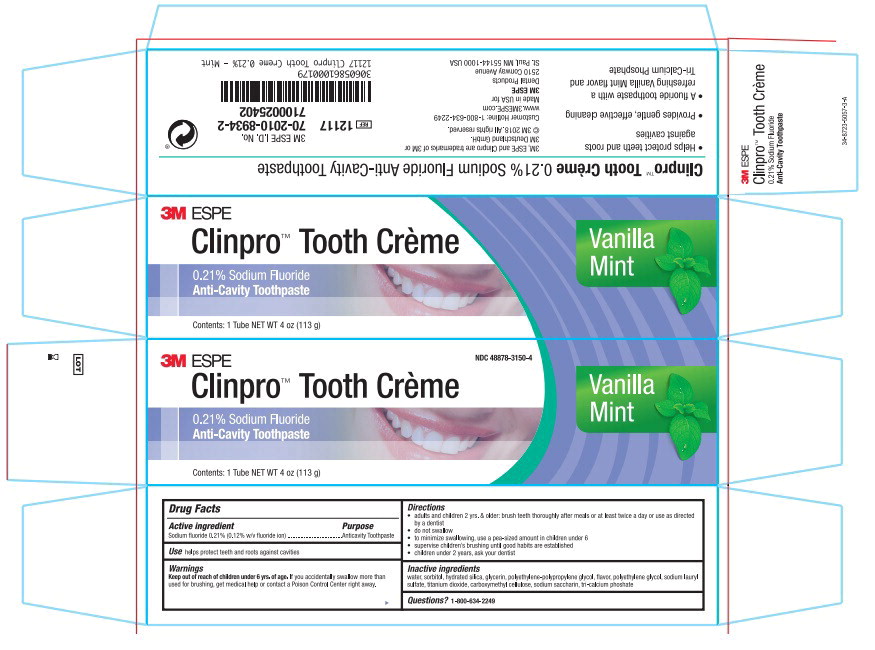 DRUG LABEL: Clinpro Tooth Creme
NDC: 48878-3150 | Form: PASTE, DENTIFRICE
Manufacturer: Solventum US LLC
Category: otc | Type: HUMAN OTC DRUG LABEL
Date: 20240801

ACTIVE INGREDIENTS: sodium fluoride 0.950 mg/1 g
INACTIVE INGREDIENTS: Water; Sorbitol; Silicon Dioxide; Glycerin; Polyethylene Glycol, Unspecified; Sodium Lauryl Sulfate; Titanium Dioxide; Carboxymethylcellulose Sodium; Saccharin Sodium; Tricalcium Phosphate

Drug Facts

Active ingredient

Sodium fluoride 0.21% (0.12% w/v fluoride ion)

Purpose

Anticavity Toothpaste

Use

helps protect teeth and roots against cavities

Warnings

Keep out of reach of children under 6 years of age. If you accidentally swallow more than used for brushing, get medical help or contact a Poison Control Center right away.

Directions

- adults and children 2 yrs. & older: brush teeth thoroughly after meals or at least twice a day or use as directed by a dentist
- do not swallow
- to minimize swallowing, use a pea-sized amount in children under 6
- supervise children's brushing until good habits are established
- children under 2 years, ask your dentist

Inactive ingredients

water, sorbitol, hydrated silica, glycerin, polyethylene-polypropylene glycol, flavor, polyethylene glycol, sodium lauryl sulfate, titanium dioxide, carboxymethyl cellulose, sodium saccharin, tri-calcium phoshate

Principal Display Panel

NDC 48878-3150-4

3M ESPE

Clinpro™ Tooth Crème

Vanilla Mint

0.21% Sodium Flouride
Anti-Cavity Toothpaste

Contents: 1 Tube NET WT 4 oz (113 g)